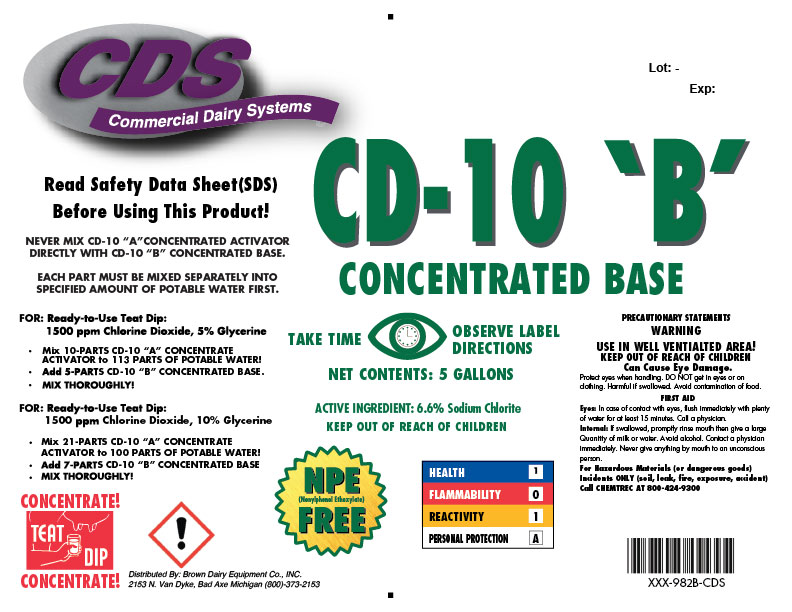 DRUG LABEL: CD-10 B Concentrated Base
NDC: 62897-982 | Form: CONCENTRATE
Manufacturer: Brown Dairy Equipment Co., Inc
Category: animal | Type: OTC ANIMAL DRUG LABEL
Date: 20190405

ACTIVE INGREDIENTS: SODIUM CHLORITE 66 g/1 L
INACTIVE INGREDIENTS: WATER; TRISODIUM NITRILOTRIACETATE

CD-10 'B' Concentrated Base

CDS Commercial Dairy Systems

WARNINGS

Read Safety Data Sheet (SDS) Before Using This Product!

WARNINGS AND PRECAUTIONS

NEVER MIX CD-10 "A" CONCENTRATED ACTIVATOR DIRECTLY WITH CD-10 "B" CONCENTRATED BASE.

EACH PART MUST BE MIXED SEPARATELY IN SPECIFIED AMOUNT OF POTABLE WATER FIRST.

FOR: Ready-to-Use Teat Dip:

1500 ppm Chlorine Dioxide, 5% Glycerine

- Mix 10-PARTS CD-10 "A" CONCENTRATE ACTIVATOR to 113 PARTS OF POTABLE WATER!
- Add 5-PARTS CD-10 "B" CONCENTRATED BASE.
- MIX THOROUGHLY!

FOR: Ready-to-use Test Dip:

1500 ppm Chlorine Dioxide, 10% Glycerine

- Mix 21-PARTS CD-10 "A" CONCENTRATE ACTIVATOR to 100 PARTS OF POTABLE WATER!
- Add 7-PARTS CD-10 "B" CONCENTRATED BASE
- MIX THOROUGHLY!

WARNINGS

CONCENTRATE!

TEAT DIP

CONCENTRATE!

PRECAUTIONS

TAKE TIME

OBSERVE LABEL DIRECTIONS

NET CONTENTS:

Lot:

Exp:

ACTIVE INGREDIENT: 6.6% Sodium Chlorite

KEEP OUT OF REACH OF CHILDREN

NPE

(Nonylphenol Ethoxylate)

FREE

HEALTH 1

FLAMMABILITY 0

REACTIVITY 1

PERSONAL PROTECTION 4

For Hazardous Materials (or dangerous goods) Incidents ONLY (soil, leak, fire, exposure, accident)

Call CHEMTREC AT 800-424-9300

PRECAUTIONS

PRECAUTIONARY STATEMENTS

WARNING

USE IN WELL VENTILATED AREA!

KEEP OUT OF REACH OF CHILDREN

Can Cause Eye Damage

Protect eye when handling. DO NOT get in eyes or on clothing. Harmful if swallowed. Avoid contamination of food.

FIRST AID

Eyes: In case of contact with eyes, flush immediately with plenty of water for at least 15 minutes. Call a physician.

Internal: If swallowed, promptly rinse mouth then give a large Quantity of milk or water. Avoid alcohol. Contact a physician immediately. Never give anything by mouth to an unconscious persom.